DRUG LABEL: Intellishade Original SPF 45
NDC: 64651-7749 | Form: CREAM
Manufacturer: Revision, LLC
Category: otc | Type: HUMAN OTC DRUG LABEL
Date: 20260112

ACTIVE INGREDIENTS: OCTINOXATE 7.5 g/100 g; OCTISALATE 5 g/100 g; TITANIUM DIOXIDE 3.5 g/100 g; ZINC OXIDE 3 g/100 g
INACTIVE INGREDIENTS: TRIETHOXYCAPRYLYLSILANE; HYDROGENATED STARCH HYDROLYSATE; GREEN TEA LEAF; TETRADECYL AMINOBUTYROYLVALYLAMINOBUTYRIC UREA TRIFLUOROACETATE; CYCLOPENTASILOXANE; HYDROLYZED JOJOBA ESTERS; ALOE VERA LEAF; BETULA PUBESCENS BARK; WHITE WAX; DIMETHICONE; SQUALANE; .ALPHA.-TOCOPHEROL ACETATE; TETRAHEXYLDECYL ASCORBATE; .ALPHA.-TOCOPHEROL; PALMITOYL TRIPEPTIDE-5; HYDROGENATED CASTOR OIL; LECITHIN, SOYBEAN; PALMITOYLLYSYLVALYLDIAMINOBUTYROYLTHREONINE; GLYCERYL CAPRYLATE; YEAST; BORON NITRIDE; EPIGALLOCATECHIN GALLATE; UBIDECARENONE; SIMMONDSIA CHINENSIS SEED; SODIUM CHLORIDE; PHENOXYETHANOL; GLYCERYL ISOSTEARATE; CHLORPHENESIN; POLYHYDROXYSTEARIC ACID (2300 MW); XANTHAN GUM; MAGNESIUM CHLORIDE; BENZOIC ACID; SORBIC ACID; POLYGLYCERYL-4 ISOSTEARATE; WATER; ETHYLHEXYL STEARATE; CETYL PEG/PPG-10/1 DIMETHICONE (HLB 5); HEXYL LAURATE; GLYCERIN; BUTYLENE GLYCOL; CETYL DIMETHICONE 25; CAPRYLIC/CAPRIC ACID

Intellishade Original SPF 45

1.7oz Revision Intellishade® Original

ITO_carton_retail_IOC9_V4_OL.jpg

ITO_tube_retail_IOR5_V3_OL.jpg

Intellishade®
Original

anti-aging
tinted moisturizer
with sunscreen

Broad-Spectrum
SPF 45

NET WT 1.7 OZ | 48 g

Active ingredient Purpose
Octinoxate 7.5% ............ Sunscreen
Octisalate 5% ................ Sunscreen
Titanium Dioxide 3.5%... Sunscreen
Zinc Oxide 3% ............... Sunscreen

Uses
• helps prevent sunburn
• if used as directed with other sun protection measures (see Directions), decreases the risk of skin cancer
and early skin aging caused by the sun

Warnings
For external use only

Do not useon damaged or broken skin

WHEN USING

When using this productkeep out of eyes. Rinse with water to remove.

Stop use and ask a doctorif rash occurs

Keep out of reach of children.If swallowed, get medical help or contact a Poison Control Center right away.

Directions
• apply liberally 15 minutes before sun exposure
• reapply at least every 2 hours
• use a water resistant sunscreen if swimming or sweating
• Sun Protection Measures.
Spending time in the sun increases your risk of skin cancer and early skin aging. To decrease
this risk, regularly use a sunscreen with a Broad-Spectrum SPF value of 15 or higher and
other sun protection measures including:
• limit time in the sun, especially from 10 a.m. – 2 p.m.
• wear long-sleeved shirts, pants, hats, and sunglasses
• children under 6 months: Ask a doctor

Inactive ingredients

Water (Aqua), Cyclopentasiloxane, Jojoba Esters, Hydrogenated Starch Hydrolysate, Caprylic/Capric Triglyceride, Glycerin, Cetyl PEG/PPG-10/1 Dimethicone, Hexyl Laurate, Polyglyceryl-4 Isostearate, Butylene Glycol, Cetyl Dimethicone, Ethylhexyl Palmitate, Ethylhexyl Stearate, Aloe Barbadensis Leaf Juice, Betula Alba Bark Extract, Camellia Sinensis Leaf Extract, Plankton Extract, Beeswax (Cera Alba), Squalane, Tocopheryl Acetate, Tetrahexyldecyl Ascorbate, Tocopherol, Palmitoyl Tripeptide-5, Hydrogenated Castor Oil, Lecithin, Palmitoyl Dipeptide-5 Diaminobutyroyl Hydroxythreonine, Glyceryl Caprylate, Tetradecyl Aminobutyroylvalylaminobutyric Urea Acetate, Yeast Extract (Faex), Boron Nitride, Epigallocatechin Gallate, Ubiquinone, Simmondsia Chinensis (Jojoba) Meal Extract, Sodium Chloride, Phenoxyethanol, Glyceryl Isostearate, Chlorphenesin, Polyhydroxystearic Acid, Xanthan Gum, Magnesium Chloride, Triethoxycaprylylsilane, Benzoic Acid, Sorbic Acid, Iron Oxides (CI 77491, CI 77492, CI 77499)

Other information
• protect this product from excessive heat and direct sun

Dist. by Revision, LP
Irving, TX 75063 Made in U.S.A.

8oz Revision Intellishade® Original

ITO_pro_tube_IOP6_V2_OL.jpg

Intellishade®
Original

anti-aging
tinted moisturizer
with sunscreen

Broad-Spectrum
SPF 45

NET WT 8 OZ | 227 g

Active ingredient Purpose
Octinoxate 7.5% ............ Sunscreen
Octisalate 5% ................ Sunscreen
Titanium Dioxide 3.5%... Sunscreen
Zinc Oxide 3% ............... Sunscreen

Uses
• helps prevent sunburn
• if used as directed with other sun protection measures (see Directions), decreases the risk of skin cancer
and early skin aging caused by the sun

Warnings
For external use only

Do not useon damaged or broken skin

WHEN USING

When using this productkeep out of eyes. Rinse with water to remove.

Stop use and ask a doctorif rash occurs

Keep out of reach of children.If swallowed, get medical help or contact a Poison Control Center right away.

Directions
• apply liberally 15 minutes before sun exposure
• reapply at least every 2 hours
• use a water resistant sunscreen if swimming or sweating
• Sun Protection Measures.
Spending time in the sun increases your risk of skin cancer and early skin aging. To decrease
this risk, regularly use a sunscreen with a Broad-Spectrum SPF value of 15 or higher and
other sun protection measures including:
• limit time in the sun, especially from 10 a.m. – 2 p.m.
• wear long-sleeved shirts, pants, hats, and sunglasses
• children under 6 months: Ask a doctor

Inactive ingredients

Water (Aqua), Cyclopentasiloxane, Jojoba Esters, Hydrogenated Starch Hydrolysate, Caprylic/Capric Triglyceride, Glycerin, Cetyl PEG/PPG-10/1 Dimethicone, Hexyl Laurate, Polyglyceryl-4 Isostearate, Butylene Glycol, Cetyl Dimethicone, Ethylhexyl Palmitate, Ethylhexyl Stearate, Aloe Barbadensis Leaf Juice, Betula Alba Bark Extract, Camellia Sinensis Leaf Extract, Plankton Extract, Beeswax (Cera Alba), Squalane, Tocopheryl Acetate, Tetrahexyldecyl Ascorbate, Tocopherol, Palmitoyl Tripeptide-5, Hydrogenated Castor Oil, Lecithin, Palmitoyl Dipeptide-5 Diaminobutyroyl Hydroxythreonine, Glyceryl Caprylate, Tetradecyl Aminobutyroylvalylaminobutyric Urea Acetate, Yeast Extract (Faex), Boron Nitride, Epigallocatechin Gallate, Ubiquinone, Simmondsia Chinensis (Jojoba) Meal Extract, Sodium Chloride, Phenoxyethanol, Glyceryl Isostearate, Chlorphenesin, Polyhydroxystearic Acid, Xanthan Gum, Magnesium Chloride, Triethoxycaprylylsilane, Benzoic Acid, Sorbic Acid, Iron Oxides (CI 77491, CI 77492, CI 77499)

Other information
• protect this product from excessive heat and direct sun

Dist. by Revision, LP
Irving, TX 75063 Made in U.S.A.

DOSAGE AND ADMINISTRATION

- apply liberally 15 minutes before sun exposure
- reapply at least every two hours
- use a water resistant sunscreen if swimming or sweating

PURPOSE

Anti-aging untinted daily moisturizer with 100% mineral sunscreen

Broad Spectrum

SPF 50